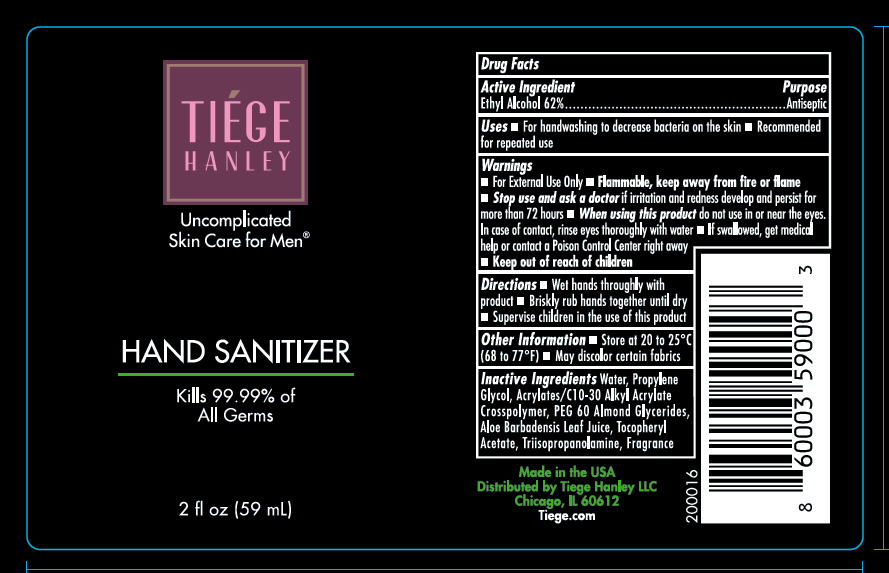 DRUG LABEL: Antibacterial Hand Sanitizer
NDC: 71714-059 | Form: GEL
Manufacturer: Tiege Hanley
Category: otc | Type: HUMAN OTC DRUG LABEL
Date: 20200327

ACTIVE INGREDIENTS: alcohol 62 mL/100 mL
INACTIVE INGREDIENTS: Propylene Glycol; water; PEG-60 ALMOND GLYCERIDES; aloe vera leaf; .Alpha.-Tocopherol Acetate; triisopropanolamine; CARBOMER INTERPOLYMER TYPE B (ALLYL PENTAERYTHRITOL CROSSLINKED)

Antibacterial Hand Sanitizer

Drug Facts

Active Ingredient

Ethyl Alcohol 62%

Purpose

Antiseptic

Uses

- for hand washing to decrease bacteria on the skin
- recommended for repeated use

Warnings

For external use only.

Flammable. Keep away from fire or flame.

When using this product do not use in or around the eyes. In case of contact, rinse eyes thoroughly with water.

Stop use and ask a doctor if irritation and redness develop and persist for more than 72 hours.

KEEP OUT OF REACH OF CHILDREN

If swallowed get medical help or contact poison control center right away.

Keep Out of reach of children.

Directions

- wet hands thoroughly with product
- briskly rub hands together until dry
- Supervise children in the use of this product.

Other Information

- store at 20-25° C (68 to 77°F)
- may discolor certain fabrics

Inactive Ingredients

Water, Propylene Glycol, Acrylates/C10-3- Alkyl Acrylate Crosspolymer, Peg-60, Almond Glycerides, Aloe Barbadensis Leaf Juice, Tocopheryl Acetate, Triisopropanolamine, Fragrance

Distributed by Tiege Hanley LLC
Chicago, IL 60612

PRINCIPAL DISPLAY PANEL - 59 mL Bottle Label

TIÉGE
HANLEY

Uncomplicated
Skin Care for Men®

HAND SANITIZER

Kills 99.99% of
All Germs

2 fl oz (59 mL)